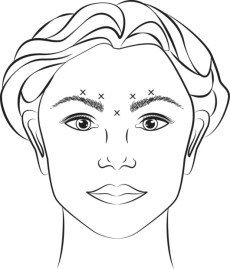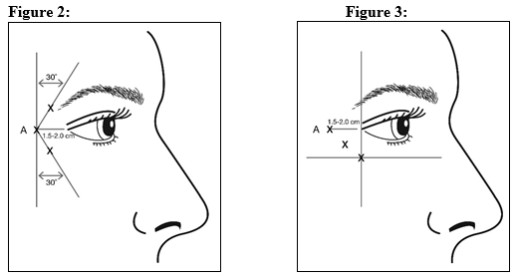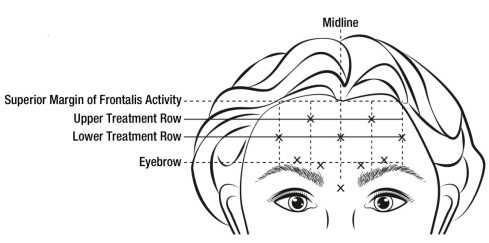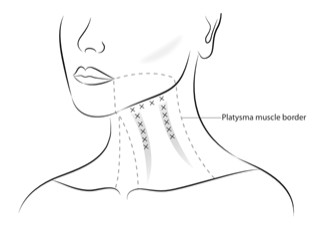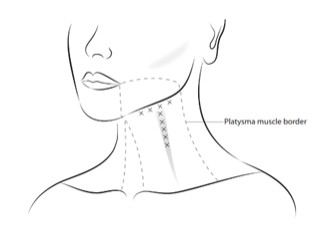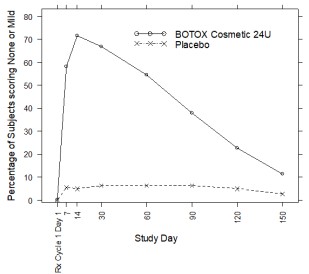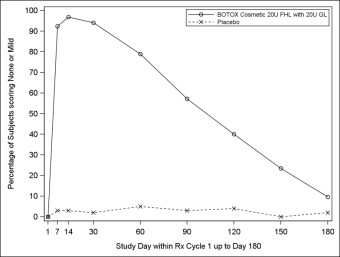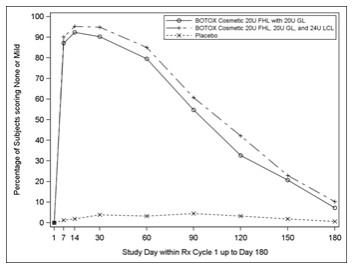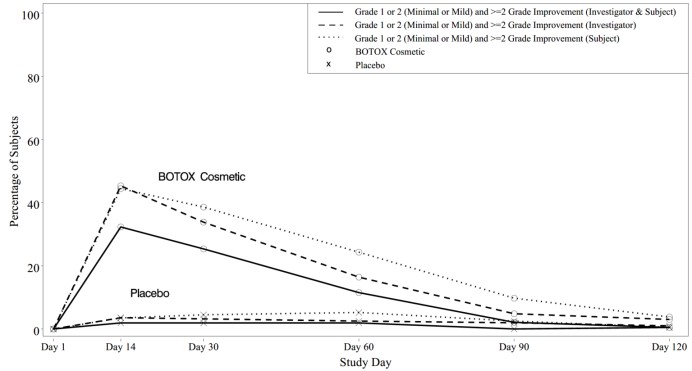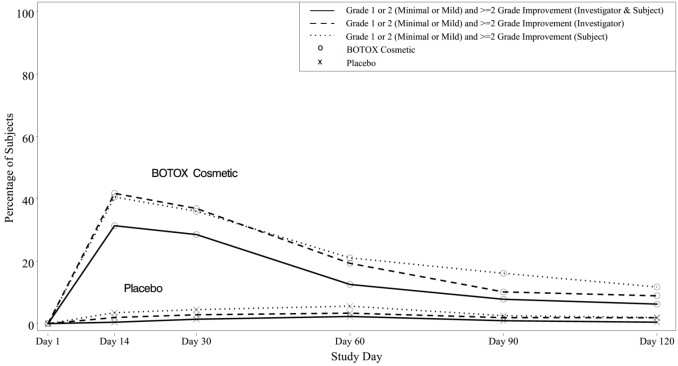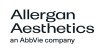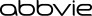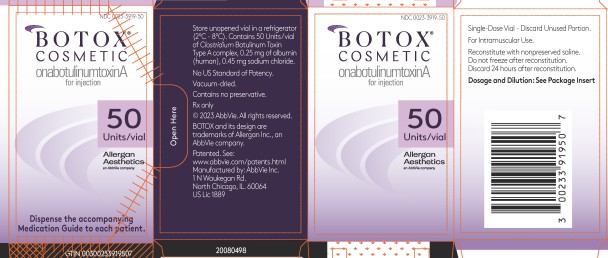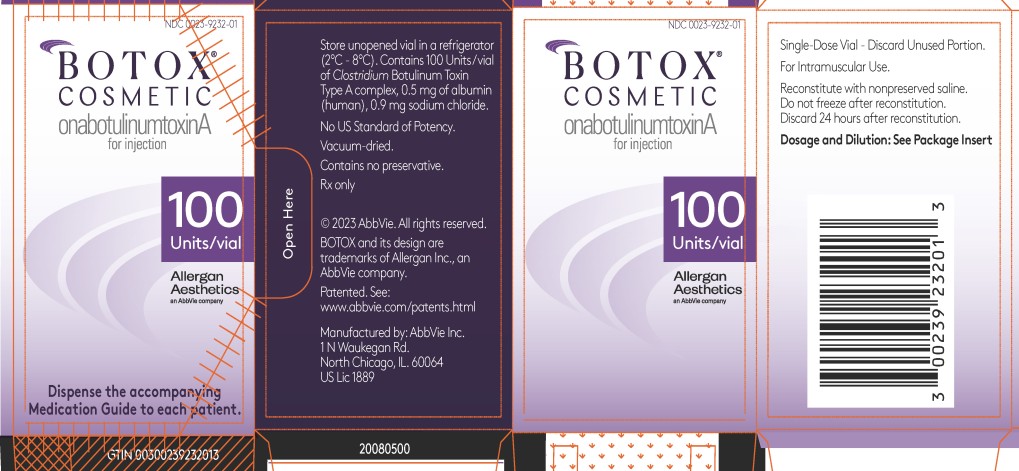 DRUG LABEL: BOTOX Cosmetic
NDC: 0023-3919 | Form: INJECTION, POWDER, LYOPHILIZED, FOR SOLUTION
Manufacturer: Allergan, Inc.
Category: prescription | Type: HUMAN PRESCRIPTION DRUG LABEL
Date: 20241018

ACTIVE INGREDIENTS: BOTULINUM TOXIN TYPE A 50 [USP'U]/1 1
INACTIVE INGREDIENTS: ALBUMIN HUMAN 0.25 mg/1 1; SODIUM CHLORIDE 0.45 mg/1 1

HIGHLIGHTS OF PRESCRIBING INFORMATION

These highlights do not include all the information needed to use BOTOX Cosmetic safely and effectively. See full prescribing information for BOTOX Cosmetic.
BOTOX® Cosmetic (onabotulinumtoxinA) for injection,
for intramuscular use
Initial U.S. Approval: 1989

RECENT MAJOR CHANGES

Indications and Usage (1) | 10/2024
Dosage and Administration (2.2, 2.3, 2.4) | 10/2024

WARNING: DISTANT SPREAD OF TOXIN EFFECT

See full prescribing information for complete boxed warning.

The effects of BOTOX Cosmetic and all botulinum toxin products may spread from the area of injection to produce symptoms consistent with botulinum toxin effects. These symptoms have been reported hours to weeks after injection. Swallowing and breathing difficulties can be life threatening and there have been reports of death. The risk of symptoms is probably greatest in children treated for spasticity but symptoms can also occur in adults, particularly in those patients who have an underlying condition that would predispose them to these symptoms. (5.2)

1 INDICATIONS AND USAGE

BOTOX Cosmetic is an acetylcholine release inhibitor and a neuromuscular blocking agent indicated in adult patients for the temporary improvement in the appearance of (1):

- Moderate to severe glabellar lines associated with corrugator and/or procerus muscle activity
- Moderate to severe lateral canthal lines associated with orbicularis oculi activity
- Moderate to severe forehead lines associated with frontalis muscle activity
- Moderate to severe platysma bands associated with platysma muscle activity

2 DOSAGE AND ADMINISTRATION

- Glabellar Lines Administration: 0.1 mL (4 Units) into each of 5 sites, for a total dose of 20 Units (2.4)
- Lateral Canthal Lines Administration: 0.1 mL (4 Units) into each of 3 sites per side (6 total injection points), for a total of 24 Units (2.4)
- Forehead Lines Administration: 0.1 mL (4 Units) into each of 5 forehead line sites (20 Units) with 0.1 mL (4 Units) into each of 5 glabellar line sites (20 Units), for a recommended total of 40 Units (2.4)
- Platysma Bands Administration: 0.05 mL (2 Units) into each of 4 sites in the upper segment of the platysma muscles, below the jawline on each side and 0.025 mL (1 Unit) into 5 sites on each vertical neck band per side (1 to 2 bands per side) for a total of 26 Units, 31 Units, or 36 Units (18, 23, or 28 injection sites, respectively) (2.4)
- BOTOX Cosmetic is administered by intramuscular injection (2.2)
- Follow dosage and administration recommendations. Do not exceed the maximum recommended cumulative dose in a treatment session for any indication (2.1, 2.2)
- See Preparation and Reconstitution Instructions for information on BOTOX Cosmetic reconstitution, storage, and preparation before injection (2.3)

3 DOSAGE FORMS AND STRENGTHS

For Injection: 50 Units or 100 Units vacuum-dried powder in a single-dose vial for reconstitution (3)

4 CONTRAINDICATIONS

- Hypersensitivity to any botulinum toxin preparation or to any of the components in the formulation (4.1, 5.4)
- Infection at the injection site (4.2)

5 WARNINGS AND PRECAUTIONS

- Potency Units of BOTOX Cosmetic cannot be compared to or converted into Units of any other preparations of botulinum toxin products (5.1, 11)
- Spread of toxin effects; swallowing and breathing difficulties can lead to death. Seek immediate medical attention if respiratory, speech or swallowing difficulties occur (5.2, 5.7)
- Potential serious adverse reactions after administration of BOTOX for unapproved uses (5.3)
- Adverse event reports have been received involving the cardiovascular system, some with fatal outcomes. Use caution when administering to patients with pre-existing cardiovascular disease. (5.5)
- Concomitant neuromuscular disorder may exacerbate clinical effects of treatment (5.6)
- Use with caution in patients with compromised respiratory function or dysphagia (5.7)

6 ADVERSE REACTIONS

The most common adverse reactions are (6.1):

- Glabellar Lines: eyelid ptosis (3%)
- Lateral Canthal Lines: eyelid edema (1%)
- Forehead Lines: headache (9%) and brow ptosis (2%)

To report SUSPECTED ADVERSE REACTIONS, contact AbbVie at 1-800-678-1605 or FDA at 1-800-FDA-1088 or www.fda.gov/medwatch.

7 DRUG INTERACTIONS

Patients receiving concomitant treatment of BOTOX Cosmetic and aminoglycosides or other agents interfering with neuromuscular transmission (e.g., curare-like agents), or muscle relaxants, should be observed closely because the effect of BOTOX Cosmetic may be potentiated (7)

FULL PRESCRIBING INFORMATION

WARNING: DISTANT SPREAD OF TOXIN EFFECT

Postmarketing reports indicate that the effects of BOTOX Cosmetic and all botulinum toxin products may spread from the area of injection to produce symptoms consistent with botulinum toxin effects. These may include asthenia, generalized muscle weakness, diplopia, ptosis, dysphagia, dysphonia, dysarthria, urinary incontinence and breathing difficulties. These symptoms have been reported hours to weeks after injection. Swallowing and breathing difficulties can be life threatening and there have been reports of death. The risk of symptoms is probably greatest in children treated for spasticity but symptoms can also occur in adults treated for spasticity and other conditions, particularly in those patients who have an underlying condition that would predispose them to these symptoms. In unapproved uses and in approved indications, cases of spread of effect have been reported at doses comparable to those used to treat cervical dystonia and spasticity and at lower doses. [see Warnings and Precautions (5.2)]

1 INDICATIONS AND USAGE

BOTOX Cosmetic (onabotulinumtoxinA) is indicated in adult patients for the temporary improvement in the appearance of:

• moderate to severe glabellar lines associated with corrugator and/or procerus muscle activity

• moderate to severe lateral canthal lines associated with orbicularis oculi activity

• moderate to severe forehead lines associated with frontalis muscle activity

• moderate to severe platysma bands associated with platysma muscle activity

2 DOSAGE AND ADMINISTRATION

2.1 Instructions for Safe Use

The potency Units of BOTOX Cosmetic (onabotulinumtoxinA) for injection are specific to the preparation and assay method utilized. BOTOX Cosmetic is not equivalent to other preparations of botulinum toxin products, and therefore, units of biological activity of BOTOX Cosmetic cannot be compared to nor converted into units of any other botulinum toxin products assessed with any other specific assay method [see Warnings and Precautions (5.1) and Description (11)].

Follow indication specific dosage and administration recommendations. Do not exceed the maximum recommended cumulative dose in a treatment session for any indication.

The safe and effective use of BOTOX Cosmetic depends upon proper storage of the product, selection of the correct dose, and proper reconstitution and administration techniques. Physicians administering BOTOX Cosmetic must understand the relevant neuromuscular and structural anatomy of the area involved and any alterations to the anatomy due to prior surgical procedures and disease.

Do not use BOTOX Cosmetic and contact AbbVie (1-800-678-1605) if:

- The tamper evident features on the carton appear to be broken or compromised, or
- The U.S. License number 1889 is not present on the vial label and carton labeling [see How Supplied/Storage and Handling (16)]

2.2 Recommended Dose

The total recommended dose in adult patients by treatment area is shown in Table 1. BOTOX Cosmetic is administered by intramuscular injection.

Table 1: Total Recommended Treatment Dose
Treatment Area | Total Recommended Treatment Dose
Glabellar lines | 20 Units in 0.5 mL
Lateral canthal lines | 24 Units in 0.6 mL
Forehead lines and glabellar lines | 40 Units in 1 mL
Platysma bands | One band on each side: 26 Units in 0.65 mL 1 band on one side, 2 bands on the other side: 31 Units in 0.78 mL Two bands on each side: 36 Units in 0.9 mL

The safety and effectiveness of dosing with BOTOX Cosmetic more frequently than every 3 months have not been clinically evaluated.

2.3 Preparation and Reconstitution Instructions

BOTOX Cosmetic is supplied in single-dose 50 Units and 100 Units per vial. Prior to intramuscular injection, reconstitute each vacuum-dried vial of BOTOX Cosmetic with sterile, preservative-free 0.9% Sodium Chloride Injection USP (see Table 2). Draw up the proper amount of diluent in the appropriate size needle and syringe to obtain a reconstituted solution at a concentration of 4 Units/0.1 mL.

Table 2: Dilution Instructions for BOTOX Cosmetic Vials (50 Units and 100 Units)
Vial | Amount of Diluent* Added | Resulting Dose Units per 0.1 mL
50 Units | 1.25 mL | 4 Units
100 Units | 2.5 mL | 4 Units

*Preservative-free 0.9% Sodium Chloride Injection, USP Only

Slowly inject the diluent into the vial. Discard the vial if a vacuum does not pull the diluent into the vial. Gently mix BOTOX Cosmetic with the saline by rotating the vial. Record the date and time of reconstitution on the space on the label. Administer BOTOX Cosmetic within 24 hours after reconstitution. During this time period, store reconstituted BOTOX Cosmetic in a refrigerator at 2°C to 8°C (36°F to 46°F). Do not freeze reconstituted BOTOX Cosmetic. BOTOX Cosmetic vials are for single-dose only. Discard any remaining solution.

Reconstituted BOTOX Cosmetic is clear, colorless to slightly yellow solution, and free of particulate matter. Parenteral drug products should be inspected visually for particulate matter and discoloration prior to administration and whenever the solution and the container permit. Do not use if the solution is cloudy or contains flakes or particles.

2.4 Administration

Draw properly reconstituted toxin into the sterile syringe, preferably a tuberculin syringe, and expel any air bubbles in the syringe barrel (see Table 3). Remove the needle used to reconstitute the product and attach a 30-33 gauge needle. Confirm the patency of the needle.

Table 3: Amount of Reconstituted Toxin to Draw Per Treatment Area
Treatment Area | Amount of Reconstituted Toxin to Draw
Glabellar lines | At least 0.5 mL
Lateral canthal lines | At least 0.6 mL
Forehead lines and glabellar lines | At least 1 mL
Platysma bands | - 1 band on each side: At least 0.65 mL - 1 band on one side, 2 bands on the other side: At least 0.78 mL - 2 bands on each side: At least 0.9 mL

Glabellar Lines

An effective dose for facial lines is determined by gross observation of the patient’s ability to activate the superficial muscles injected.

In order to reduce the complication of ptosis, take the following steps:

- Avoid injection near the levator palpebrae superioris, particularly in patients with larger brow depressor complexes.
- Place lateral corrugator injections at least 1 cm above the bony supraorbital ridge.
- Ensure the injected volume/dose is accurate and where feasible kept to a minimum.
- Do not inject toxin closer than 1 cm above the central eyebrow.

Inject 4 Units (0.1 mL) of reconstituted BOTOX Cosmetic intramuscularly into each of 5 sites, 2 in each corrugator muscle and 1 in the procerus muscle for a total dose of 20 Units (see Figure 1). Typically, the initial doses of reconstituted BOTOX Cosmetic induce chemical denervation of the injected muscles one to two days after injection, increasing in intensity during the first week.

The duration of effect of BOTOX Cosmetic for glabellar lines is approximately 3-4 months.

Figure 1:

Lateral Canthal Lines

Give injections with the needle bevel tip up and oriented away from the eye. Inject 4 Units (0.1 mL) of reconstituted BOTOX Cosmetic into 3 sites per side (6 total injection points) in the lateral orbicularis oculi muscle for a total of 24 Units (0.6 mL) (12 Units per side). Administer the first injection (A) approximately 1.5-2.0 cm temporal to the lateral canthus and just temporal to the orbital rim. If the lines in the lateral canthal region are above and below the lateral canthus, inject per Figure 2. Alternatively, if the lines in the lateral canthal region are primarily below the lateral canthus, inject per Figure 3.

For simultaneous treatment with glabellar lines, the dose is 24 Units for lateral canthal lines and 20 Units for glabellar lines (see Glabellar Lines Administration and Figure 1), with a total dose of 44 Units.

Forehead Lines in Conjunction with Glabellar Lines

Treat forehead lines in conjunction with glabellar lines (see Glabellar Lines Administration and Figure 1) to minimize the potential for brow ptosis. The recommended total dose for treatment of forehead lines (20 Units [0.5 mL]) in conjunction with glabellar lines (20 Units [0.5 mL]) is 40 Units (1 mL).

When identifying the location of the appropriate injection sites in the frontalis muscle, assess the overall relationship between the size of the subject’s forehead, and the distribution of frontalis muscle activity.

Locate the following horizontal treatment rows by light palpation of the forehead at rest and maximum eyebrow elevation:

- Superior Margin of Frontalis Activity: approximately 1 cm above the most superior forehead crease
- Lower Treatment Row: midway between the superior margin of frontalis activity and the eyebrow, at least 2 cm above the eyebrow
- Upper Treatment Row: midway between the superior margin of frontalis activity and lower treatment row

Inject 4 Units (0.1 mL) of reconstituted BOTOX Cosmetic into 5 sites in the frontalis muscle, for a total of 20 Units (0.5 mL). Place the 5 injections at the intersection of the horizontal treatment rows with the following vertical landmarks (see Figure 4):

- On the lower treatment row at the midline of the face, and 0.5 – 1.5 cm medial to the palpated temporal fusion line (temporal crest); repeat for the other side.
- On the upper treatment row, midway between the lateral and medial sites on the lower treatment row; repeat for the other side.

Figure 4:

For simultaneous treatment with lateral canthal lines, the total dose is 64 Units, comprised of 20 Units for forehead lines, 20 Units for glabellar lines, and 24 Units for lateral canthal lines (see Lateral Canthal Lines Administration and Figures 2 and 3).

Platysma Bands

Using an appropriately sized sterile syringe, needle, and aseptic technique, inject 2 Units (0.05 mL) of reconstituted BOTOX Cosmetic into 4 sites in the upper segment of platysma muscle, below the jawline on each side. For each side, administer the 4 jawline injections to the upper platysma muscle approximately 1 to 2 cm inferior and parallel to the lower mandibular border. Ensure the anterior injection site is in line with the oral commissure, and the posterior injection is slightly anterior to the angle of the mandible. Administer the remaining 2 injections equidistant (approximately 1 to 2 cm apart) between the anterior and posterior injection points (see Figures 5 and 6).

In addition, inject 1 Unit (0.025 mL) of reconstituted BOTOX Cosmetic into 5 sites along each vertical neck band, 1 to 2 vertical neck bands per side. For each vertical neck band identified, 1 to 2 per side, distribute 5 injections vertically approximately 1 to 2 cm apart (see Figures 5 and 6). Ensure the most superior injection site is approximately 1 to 2 cm inferior to the jawline injections.

Depending on platysma band severity, the total dose may be 26 Units (1 band/side), 31 Units (1 band one side, 2 bands other side), or 36 Units (2 bands/side) (see Table 4 and Figures 5 and 6 below).

Figure 5: Injection Sites for Platysma Band (2 Bands) | Figure 6: Injection Sites for Platysma Band (1 Band)

Administer all platysma muscle injections superficially and intramuscularly with the needle perpendicular to the surface of the skin. For vertical neck band injections, identify each band while the patient is contracting their platysma. Gently pinch the band to isolate the muscle from nearby anatomical structures during administration (see Table 4).

To reduce injection-related complications, administer injection at least 1 cm inferior to the lower mandibular border. Do not inject into structures deep to the platysma muscle, particularly in the anterior region of the neck.

Table 4: Dosing for Platysma Bands
Platysma Bands Presentation | Jawline Injections | Neck Band Injections | Total Number of Injection Sites | Total Dose
1 band on each side | 2 Units (0.05 mL) into 4 sites per side (total of 8 sites and 16 Units) | 1 Unit (0.025 mL) into 5 sites per band (total of 10 sites and 10 Units) | 18 sites | 26 Units (0.65 mL)
1 band on one side, 2 bands on the other side | 2 Units (0.05 mL) into 4 sites per side (total of 8 sites and 16 Units) | 1 Unit (0.025 mL) into 5 sites per band (total of 15 sites and 15 Units) | 23 sites | 31 Units (0.78 mL)
2 bands on each side | 2 Units (0.05 mL) into 4 sites per side (total of 8 sites and 16 Units) | 1 Unit (0.025 mL) into 5 sites per band (total of 20 sites and 20 Units) | 28 sites | 36 Units (0.9 mL)

3 DOSAGE FORMS AND STRENGTHS

- For injection: 50 Units, vacuum-dried powder in a single-dose vial for reconstitution
- For injection: 100 Units, vacuum-dried powder in a single-dose vial for reconstitution

4 CONTRAINDICATIONS

4.1 Known Hypersensitivity to Botulinum Toxin

BOTOX Cosmetic is contraindicated in individuals with known hypersensitivity to any botulinum toxin preparation or to any of the components in the formulation [see Warnings and Precautions (5.4)].

4.2 Infection at the Injection Site(s)

BOTOX Cosmetic is contraindicated in the presence of infection at the proposed injection site(s).

5 WARNINGS AND PRECAUTIONS

5.1 Lack of Equivalency Between Botulinum Toxin Products

The potency Units of BOTOX Cosmetic are specific to the preparation and assay method utilized. BOTOX Cosmetic is not equivalent to other preparations of botulinum toxin products, and therefore, Units of biological activity of BOTOX Cosmetic cannot be compared to nor converted into Units of any other botulinum toxin products assessed with any other specific assay method [see Description (11)].

5.2 Spread of Toxin Effect

Postmarketing safety data from BOTOX Cosmetic and other approved botulinum toxins suggest that botulinum toxin effects may, in some cases, be observed beyond the site of local injection. The symptoms are consistent with the mechanism of action of botulinum toxin and may include asthenia, generalized muscle weakness, diplopia, ptosis, dysphagia, dysphonia, dysarthria, urinary incontinence, and breathing difficulties. These symptoms have been reported hours to weeks after injection. Swallowing and breathing difficulties can be life threatening and there have been reports of death related to spread of toxin effects. The risk of symptoms is probably greatest in children treated for spasticity but symptoms can also occur in adults treated for spasticity and other conditions, and particularly in those patients who have an underlying condition that would predispose them to these symptoms. In unapproved uses and in approved indications, symptoms consistent with spread of toxin effect have been reported at doses comparable to or lower than doses used to treat cervical dystonia and spasticity. Advise patients or caregivers to seek immediate medical care if swallowing, speech or respiratory disorders occur.

No definitive serious adverse event reports of distant spread of toxin effect associated with dermatologic use of BOTOX/BOTOX Cosmetic at the labeled dose of 20 Units (for glabellar lines), 24 Units (for lateral canthal lines), 40 Units (for forehead lines with glabellar lines), 44 Units (for simultaneous treatment of lateral canthal lines and glabellar lines), 64 Units (for simultaneous treatment of lateral canthal lines, glabellar lines, and forehead lines), or 100 Units (for severe primary axillary hyperhidrosis) have been reported.

No definitive serious adverse event reports of distant spread of toxin effect associated with BOTOX for blepharospasm at the recommended dose (30 Units and below), strabismus, or chronic migraine at the labeled doses have been reported.

5.3 Serious Adverse Reactions with Unapproved Use

Serious adverse reactions, including excessive weakness, dysphagia, and aspiration pneumonia, with some adverse reactions associated with fatal outcomes, have been reported in patients who received BOTOX injections for unapproved uses. In these cases, the adverse reactions were not necessarily related to distant spread of toxin, but may have resulted from the administration of BOTOX to the site of injection and/or adjacent structures. In several of the cases, patients had pre-existing dysphagia or other significant disabilities. There is insufficient information to identify factors associated with an increased risk for adverse reactions associated with the unapproved uses of BOTOX. The safety and effectiveness of BOTOX for unapproved uses have not been established.

5.4 Hypersensitivity Reactions

Serious and/or immediate hypersensitivity reactions have been reported. These reactions include anaphylaxis, serum sickness, urticaria, soft tissue edema, and dyspnea. If such a reaction occurs, discontinue further injection of BOTOX Cosmetic and immediately institute appropriate medical therapy. One fatal case of anaphylaxis has been reported in which lidocaine was used as the diluent, and consequently the causal agent cannot be reliably determined.

5.5 Cardiovascular System

There have been reports following administration of BOTOX/BOTOX Cosmetic of adverse events involving the cardiovascular system, including arrhythmia and myocardial infarction, some with fatal outcomes. Some of these patients had risk factors including pre-existing cardiovascular disease. Use caution when administering to patients with pre-existing cardiovascular disease.

5.6 Increased Risk of Clinically Significant Effects with Pre-Existing Neuromuscular Disorders

Patients with neuromuscular disorders may be at increased risk of clinically significant effects including generalized muscle weakness, diplopia, ptosis, dysphonia, dysarthria, severe dysphagia and respiratory compromise from onabotulinumtoxinA [see Warnings and Precautions (5.2, 5.7)]. Monitor individuals with peripheral motor neuropathic diseases, amyotrophic lateral sclerosis or neuromuscular junction disorders (e.g., myasthenia gravis or Lambert-Eaton syndrome) when given botulinum toxin.

5.7 Dysphagia and Breathing Difficulties

Treatment with BOTOX and other botulinum toxin products can result in swallowing or breathing difficulties. Patients with pre-existing swallowing or breathing difficulties may be more susceptible to these complications. In most cases, this is a consequence of weakening of muscles in the area of injection that are involved in breathing or oropharyngeal muscles that control swallowing or breathing [see Warnings and Precautions (5.2)].

Deaths as a complication of severe dysphagia have been reported after treatment with botulinum toxin. Dysphagia may persist for several months, and require use of a feeding tube to maintain adequate nutrition and hydration. Aspiration may result from severe dysphagia and is a particular risk when treating patients in whom swallowing or respiratory function is already compromised.

Treatment with botulinum toxins may weaken neck muscles that serve as accessory muscles of ventilation. This may result in a critical loss of breathing capacity in patients with respiratory disorders who may have become dependent upon these accessory muscles. There have been postmarketing reports of serious breathing difficulties, including respiratory failure.

Patients with smaller neck muscle mass and patients who require bilateral injections into the sternocleidomastoid muscle for the treatment of cervical dystonia have been reported to be at greater risk for dysphagia. Limiting the dose injected into the sternocleidomastoid muscle may reduce the occurrence of dysphagia. Injections into the levator scapulae may be associated with an increased risk of upper respiratory infection and dysphagia.

Patients treated with botulinum toxin may require immediate medical attention should they develop problems with swallowing, speech or respiratory disorders. These reactions can occur within hours to weeks after injection with botulinum toxin [see Warnings and Precautions (5.2)].

5.8 Pre-existing Conditions at the Injection Site

Use caution when BOTOX Cosmetic treatment is used in the presence of inflammation at the proposed injection site(s), ptosis, or when excessive weakness or atrophy is present in the targeted muscle(s).

5.9 Corneal Exposure and Ulceration in Patients Treated with BOTOX for Blepharospasm

Reduced blinking from injection of botulinum toxin products in or near the orbicularis oculi muscle can lead to corneal exposure, persistent corneal epithelial defect, and corneal ulceration, especially in patients with VII nerve disorders.

Employ vigorous treatment of any corneal epithelial defect. This may require protective drops, ointment, therapeutic soft contact lenses, or closure of the eye by patching or other means.

5.10 Dry Eye in Patients Treated with BOTOX Cosmetic

There have been reports of dry eye associated with BOTOX Cosmetic injection in or near the orbicularis oculi muscle. If symptoms of dry eye (e.g., eye irritation, photophobia, or visual changes) persist, consider referring patients to an ophthalmologist [see Warnings and Precautions (5.9)].

5.11 Spatial Disorientation, Double Vision or Past-Pointing in Patients Treated for Strabismus

Inducing paralysis in one or more extraocular muscles may produce spatial disorientation, double vision or past pointing. Covering the affected eye may alleviate these symptoms.

5.12 Human Albumin and Transmission of Viral Diseases

This product contains albumin, a derivative of human blood. Based on effective donor screening and product manufacturing processes, it carries a remote risk for transmission of viral diseases and variant Creutzfeldt-Jakob disease (vCJD). There is a theoretical risk for transmission of Creutzfeldt-Jakob disease (CJD), which would also be considered remote. No cases of transmission of viral diseases, CJD or vCJD have ever been identified for licensed albumin or albumin contained in other licensed products.

6 ADVERSE REACTIONS

The following adverse reactions to BOTOX Cosmetic (onabotulinumtoxinA) for injection are discussed in greater detail in other sections of the labeling:

- Spread of Toxin Effects [see Warnings and Precautions (5.2)]
- Hypersensitivity [see Contraindications (4.1) and Warnings and Precautions (5.4)]
- Dysphagia and Breathing Difficulties [see Warnings and Precautions (5.7)]

6.1 Clinical Trials Experience

Because clinical trials are conducted under widely varying conditions, the adverse reaction rates observed in the clinical trials of a drug cannot be directly compared to rates in the clinical trials of another drug and may not reflect the rates observed in clinical practice.

BOTOX and BOTOX Cosmetic contain the same active ingredient in the same formulation, but have different labeled Indications and Usage. Therefore, adverse events observed with the use of BOTOX also have the potential to be observed with the use of BOTOX Cosmetic.

In general, adverse reactions occur within the first week following injection of BOTOX Cosmetic and while in many cases are transient, may have a duration of several months or longer. Localized pain, infection, inflammation, tenderness, swelling, erythema, and/or bleeding/bruising may be associated with the injection. Needle-related pain and/or anxiety may result in vasovagal responses (including e.g., syncope, hypotension), which may require appropriate medical therapy.

Local weakness of the injected muscle(s) represents the expected pharmacological action of botulinum toxin. However, weakness of nearby muscles may also occur due to spread of toxin [see Warnings and Precautions (5.2)].

Glabellar Lines

Table 5 lists selected adverse reactions reported by ≥1% of BOTOX Cosmetic treated subjects (N=405) aged 18 to 75 who were evaluated in the randomized, placebo-controlled clinical studies to assess the use of BOTOX Cosmetic in the improvement of the appearance of glabellar lines.

Table 5: Adverse Reactions Reported by ≥1% of BOTOX Cosmetic treated Subjects and More Frequent than in Placebo-treated Subjects in Double-blind, Placebo-controlled Clinical Studies of Treatment of Glabellar Lines
Adverse Reactions by System Organ Class | BOTOX Cosmetic (N=405) | Placebo (N=130)
General Disorders and Administration Site Conditions Facial pain | 6 (1%) | 0 (0%)
Nervous System Disorders Facial paresis | 5 (1%) | 0 (0%)
Eye Disorders Eyelid ptosis | 13 (3%) | 0 (0%)
Musculoskeletal and Connective Tissue Disorders Muscular Weakness | 6 (1%) | 0 (0%)

Lateral Canthal Lines

Table 6 lists selected adverse reactions reported within 90 days following injection by ≥1% of BOTOX Cosmetic treated subjects (N=526) aged 18 to 75 who were evaluated in two randomized, double-blind, placebo-controlled clinical studies to assess the use of BOTOX Cosmetic in the improvement of the appearance of lateral canthal lines alone.

Table 6: Adverse Reaction Reported by ≥1% of BOTOX Cosmetic Treated Subjects and More Frequent than in Placebo-treated Subjects Within 90 Days, in Double-blind, Placebo-controlled Clinical Studies of Treatment of Lateral Canthal Lines
Adverse Reactions by System Organ Class | BOTOX Cosmetic 24 Units (N=526) | Placebo (N=530)
Eye disorders Eyelid edema | 5 (1%) | 0 (0%)

Forehead Lines

Table 7 lists selected adverse reactions reported by ≥1% of BOTOX Cosmetic treated subjects (N=665) aged 18 to 77 who were evaluated in two randomized, double-blind, placebo-controlled clinical studies to assess the use of BOTOX Cosmetic in the improvement of the appearance of forehead lines with glabellar lines.

Table 7: Adverse Reactions Reported by ≥1% of BOTOX Cosmetic treated Subjects More Frequently than in Placebo-treated Subjects, in Double-blind, Placebo-controlled Clinical Studies of Treatment of Forehead Lines
Adverse Reactions by System Organ Class | BOTOX Cosmetic (20 Units forehead lines with 20 Units glabellar lines) (N=665) | Placebo (N=315)
Nervous System Disorders Headache | 58 (9%) | 17 (5%)
Eye Disorders Eyelid ptosis | 12 (2%) | 1 (0%)
Skin and Subcutaneous Tissue Disorders Brow ptosis Skin tightness | 13 (2%) 10 (2%) | 0 (0%) 0 (0%)

There were no additional adverse drug reactions reported with the simultaneous treatment of forehead lines, glabellar lines, and lateral canthal lines.

Platysma Bands

The safety of BOTOX Cosmetic (26 Units, 31 Units, or 36 Units) was evaluated in two double-blind, placebo-controlled, clinical trials with 407 BOTOX Cosmetic-treated subjects and 425 subjects receiving placebo.

The safety profile of BOTOX Cosmetic treatment of platysma bands is consistent with the known safety profile of BOTOX Cosmetic for other indications.

6.2 Postmarketing Experience

Because these reactions are reported voluntarily from a population of uncertain size, it is not always possible to reliably estimate their frequency or establish a causal relationship to drug exposure.

There have been spontaneous reports of death, sometimes associated with dysphagia, pneumonia, and/or other significant debility or anaphylaxis, after treatment with botulinum toxin [see Warnings and Precautions (5.4, 5.7)].

There have also been reports of adverse events involving the cardiovascular system, including arrhythmia and myocardial infarction, some with fatal outcomes. Some of these patients had risk factors including cardiovascular disease.

New onset or recurrent seizures have also been reported, typically in patients who are predisposed to experiencing these events.

The following adverse reactions by System Organ Class have been identified during post-approval use of BOTOX/BOTOX Cosmetic:

Ear and labyrinth disorders

Hypoacusis; tinnitus; vertigo

Eye disorders

Diplopia; dry eye; eyelid edema; lagophthalmos; strabismus; visual disturbances; vision blurred

Gastrointestinal disorders

Abdominal pain; diarrhea; dry mouth; nausea; vomiting

General disorders and administration site conditions

Denervation; malaise; pyrexia

Metabolism and nutrition disorders

Anorexia

Musculoskeletal and connective tissue disorders

Localized muscle twitching/involuntary muscle contractions; Mephisto sign; muscle atrophy; myalgia

Nervous system disorders

Brachial plexopathy; dysarthria; facial palsy; hypoaesthesia; localized numbness; myasthenia gravis; paresthesia; peripheral neuropathy; radiculopathy; syncope

Respiratory, thoracic and mediastinal disorders

Aspiration pneumonia; dyspnea; respiratory depression and/or respiratory failure

Skin and subcutaneous tissue disorders

Alopecia, including madarosis; hyperhidrosis; pruritus; skin rash (including erythema multiforme, dermatitis psoriasiform, and psoriasiform eruption)

7 DRUG INTERACTIONS

No formal drug interaction studies have been conducted with BOTOX Cosmetic (onabotulinumtoxinA) for injection.

7.1 Aminoglycosides and Other Agents Interfering with Neuromuscular Transmission

Co-administration of BOTOX Cosmetic and aminoglycosides or other agents interfering with neuromuscular transmission (e.g., curare-like compounds) should only be performed with caution as the effect of the toxin may be potentiated.

7.2 Anticholinergic Drugs

Use of anticholinergic drugs after administration of BOTOX Cosmetic may potentiate systemic anticholinergic effects.

7.3 Other Botulinum Neurotoxin Products

The effect of administering different botulinum neurotoxin products at the same time or within several months of each other is unknown. Excessive neuromuscular weakness may be exacerbated by administration of another botulinum toxin prior to the resolution of the effects of a previously administered botulinum toxin.

7.4 Muscle Relaxants

Excessive weakness may also be exaggerated by administration of a muscle relaxant before or after administration of BOTOX Cosmetic.

8 USE IN SPECIFIC POPULATIONS

8.1 Pregnancy

Risk Summary

There are no studies or adequate data from postmarketing surveillance on the developmental risk associated with use of BOTOX Cosmetic in pregnant women.

In animal studies, administrations of BOTOX Cosmetic during pregnancy resulted in adverse effects on fetal growth (decreased fetal body weight and skeletal ossification) at clinically relevant doses, which were associated with maternal toxicity [see Data].

The background risk of major birth defects and miscarriage for the indicated populations is unknown. All pregnancies have a background risk of birth defect, loss or other adverse outcomes. In the U.S. general population, the estimated background risk of major birth defects and miscarriages in clinically recognized pregnancies is 2-4% and 15-20%, respectively.

Data

Animal Data

When BOTOX Cosmetic (4, 8, or 16 Units/kg) was administered intramuscularly to pregnant mice or rats two times during the period of organogenesis (on gestation days 5 and 13), reductions in fetal body weight and decreased fetal skeletal ossification were observed at the two highest doses. The no-effect dose for developmental toxicity in these studies (4 Units/kg) is approximately 4 times the average high human dose for glabellar lines, lateral canthal lines, and forehead lines of 64 Units on a body weight basis (Units/kg).

When BOTOX Cosmetic was administered intramuscularly to pregnant rats (0.125, 0.25, 0.5, 1, 4, or 8 Units/kg) or rabbits (0.063, 0.125, 0.25, or 0.5 Units/kg) daily during the period of organogenesis (total of 12 doses in rats, 13 doses in rabbits), reduced fetal body weights and decreased fetal skeletal ossification were observed at the two highest doses in rats and at the highest dose in rabbits. These doses were also associated with significant maternal toxicity, including abortions, early deliveries, and maternal death. The developmental no-effect doses in these studies of 1 Unit/kg in rats is approximately equal the average high human dose of 64 Units based on Units/kg, and the developmental no-effect dose of 0.25 Units/kg in rabbits is less than the average high human dose based on Units/kg.

When pregnant rats received single intramuscular injections (1, 4, or 16 Units/kg) at three different periods of development (prior to implantation, implantation, or organogenesis), no adverse effects on fetal development were observed. The developmental no-effect level for a single maternal dose in rats (16 Units/kg) is approximately 16 times the average high human dose of 64 Units based on Units/kg.

8.2 Lactation

Risk Summary

There are no data on the presence of BOTOX Cosmetic in human or animal milk, the effects on the breastfed child, or the effects on milk production.

The developmental and health benefits of breastfeeding should be considered along with the mother’s clinical need for BOTOX Cosmetic and any potential adverse effects on the breastfed infant from BOTOX Cosmetic or from the underlying maternal conditions.

8.4 Pediatric Use

The safety and effectiveness of BOTOX Cosmetic have not been established in pediatric patients.

8.5 Geriatric Use

Glabellar Lines

In the two initial glabellar lines clinical studies of BOTOX Cosmetic, the responder rates appeared to be higher for subjects younger than age 65 than for subjects 65 years or older [see Clinical Studies (14)].

Lateral Canthal Lines

In the two lateral canthal lines clinical studies of BOTOX Cosmetic, the responder rates appeared to be higher for subjects younger than age 65 than for subjects 65 years or older.

Forehead Lines

In the two forehead lines clinical studies of BOTOX Cosmetic, the responder rates appeared to be higher for subjects younger than age 65 than for subjects 65 years or older.

Platysma Bands

In the two platysma bands clinical studies of BOTOX Cosmetic, 3.6% of subjects (13 subjects) treated with BOTOX Cosmetic were 65 years or older. Although the responder rates appeared to be higher for subjects younger than age 65 than for subjects 65 years or older, clinical studies of BOTOX Cosmetic did not include sufficient numbers of subjects 65 years or older to determine whether they respond differently from younger subjects.

10 OVERDOSAGE

Excessive doses of BOTOX Cosmetic (onabotulinumtoxinA) for injection may be expected to produce neuromuscular weakness with a variety of symptoms.

Symptoms of overdose are likely not to be present immediately following injection. Should accidental injection or oral ingestion occur or overdose be suspected, consider patients for further medical evaluation and immediately institute appropriate medical therapy, which may include hospitalization. The patient should be medically supervised for several weeks for signs and symptoms of systemic muscular weakness which could be local, or distant from the site of injection [see Boxed Warning and Warnings and Precautions (5.2, 5.7)].

If the musculature of the oropharynx and esophagus are affected, aspiration may occur which may lead to development of aspiration pneumonia. If the respiratory muscles become paralyzed or sufficiently weakened, intubation and assisted respiration may be necessary until recovery takes place. Supportive care could involve the need for a tracheostomy and/or prolonged mechanical ventilation, in addition to other general supportive care.

In the event of overdose, antitoxin raised against botulinum toxin is available from the Centers for Disease Control and Prevention (CDC) in Atlanta, GA. However, the antitoxin will not reverse any botulinum toxin-induced effects already apparent by the time of antitoxin administration. In the event of suspected or actual cases of botulinum toxin poisoning, please contact your local or state Health Department to process a request for antitoxin through the CDC. If you do not receive a response within 30 minutes, please contact the CDC directly at 1-770-488-7100. More information can be obtained at http://www.cdc.gov/mmwr/preview/mmwrhtml/mm5232a8.htm.

11 DESCRIPTION

BOTOX Cosmetic (onabotulinumtoxinA) for injection, is a sterile, vacuum-dried purified botulinum toxin type A, produced from fermentation of Hall strain Clostridium botulinum type A intended for intramuscular use. It is purified from the culture solution by dialysis and a series of acid precipitations to a complex consisting of the neurotoxin, and several accessory proteins. The complex is dissolved in sterile sodium chloride solution containing Albumin Human and is sterile filtered (0.2 microns) prior to filling and vacuum-drying.

The primary release procedure for BOTOX Cosmetic uses a cell-based potency assay to determine the potency relative to a reference standard. The assay is specific to AbbVie’s products BOTOX and BOTOX Cosmetic. One Unit of BOTOX Cosmetic corresponds to the calculated median intraperitoneal lethal dose (LD50) in mice. Due to specific details of this assay such as the vehicle, dilution scheme and laboratory protocols, Units of biological activity of BOTOX Cosmetic cannot be compared to nor converted into Units of any other botulinum toxin or any toxin assessed with any other specific assay method. The specific activity of BOTOX Cosmetic is approximately 20 Units/nanogram of neurotoxin complex.

Each vial of BOTOX Cosmetic contains either 50 Units of Clostridium botulinum type A neurotoxin complex, 0.25 mg of Albumin Human, and 0.45 mg of sodium chloride; or 100 Units of Clostridium botulinum type A neurotoxin complex, 0.5 mg of Albumin Human, and 0.9 mg of sodium chloride in a sterile, vacuum-dried form without a preservative.

12 CLINICAL PHARMACOLOGY

12.1 Mechanism of Action

BOTOX Cosmetic blocks neuromuscular transmission by binding to acceptor sites on motor nerve terminals, entering the nerve terminals, and inhibiting the release of acetylcholine. This inhibition occurs as the neurotoxin cleaves SNAP-25, a pre-synaptic protein integral to the successful docking and release of acetylcholine from vesicles situated within nerve endings. When injected intramuscularly at therapeutic doses, BOTOX Cosmetic produces partial chemical denervation of the muscle resulting in a localized reduction in muscle activity. In addition, the muscle may atrophy, axonal sprouting may occur, and extrajunctional acetylcholine receptors may develop. There is evidence that reinnervation of the muscle may occur, thus slowly reversing muscle denervation produced by BOTOX Cosmetic.

12.2 Pharmacodynamics

No formal pharmacodynamic studies have been conducted with BOTOX Cosmetic (onabotulinumtoxinA) for injection.

12.3 Pharmacokinetics

Using currently available analytical technology, it is not possible to detect BOTOX Cosmetic in the peripheral blood following intramuscular injection at the recommended doses.

12.6 Immunogenicity

Since BOTOX Cosmetic is a therapeutic protein, there is a potential for immunogenicity. The detection of antibody formation is highly dependent on the sensitivity and specificity of the assay. Additionally, the observed incidence of antibody (including neutralizing antibody) positivity in an assay may be influenced by several factors including assay methodology, sample handling, timing of sample collection, concomitant medications, and underlying disease. For these reasons, comparison of the incidence of antibodies to BOTOX Cosmetic in the studies described below with the incidence of antibodies in other studies or to other products may be misleading.

In three Lateral Canthal Line trials, 916 subjects (517 subjects at 24 Units and 399 subjects at 44 Units) treated with BOTOX Cosmetic had specimens analyzed for antibody formation. Among the 916 BOTOX Cosmetic treated subjects, 14 subjects (1.5%) developed binding antibodies and no subjects (0%) developed the presence of neutralizing antibodies.

The data reflect the subjects whose test results were considered positive or negative for neutralizing activity to BOTOX Cosmetic in a mouse protection assay.

The critical factors for neutralizing antibody formation have not been well characterized. The results from some studies suggest that botulinum toxin injections at more frequent intervals or at higher doses may lead to greater incidence of antibody formation. The potential for antibody formation may be minimized by injecting with the lowest effective dose given at the longest feasible intervals between injections.

13 NONCLINICAL TOXICOLOGY

13.1 Carcinogenesis, Mutagenesis, Impairment of Fertility

Long term studies in animals have not been performed to evaluate carcinogenic potential of BOTOX Cosmetic.

BOTOX Cosmetic was negative in a battery of in vitro (microbial reverse mutation assay, mammalian cell mutation assay, and chromosomal aberration assay) and in vivo (micronucleus assay) genetic toxicologic assays.

In fertility studies of BOTOX Cosmetic (4, 8, or 16 Units/kg) in which either male or female rats were injected intramuscularly prior to mating and on the day of mating (3 doses, 2 weeks apart for males, 2 doses, 2 weeks apart for females) to untreated animals, reduced fertility was observed in males at the intermediate and high doses and in females at the high dose. The no-effect doses for reproductive toxicity (4 Units/kg in males, 8 Units/kg in females) are approximately 4-8 times the average high human dose for glabellar lines, lateral canthal lines, and forehead lines of 64 Units on a body weight basis (Units/kg).

14 CLINICAL STUDIES

14.1 Glabellar Lines

Two randomized, multi-center, double-blind, placebo-controlled studies of identical design were conducted to evaluate BOTOX Cosmetic for use in the temporary improvement of the appearance of moderate to severe glabellar facial lines. The studies enrolled healthy adults (ages 18 to 75) with glabellar lines of at least moderate severity at maximum frown. Subjects were excluded if they had ptosis, deep dermal scarring, or an inability to substantially lessen glabellar lines even by physically spreading them apart. Subjects received a single treatment with BOTOX Cosmetic (N=405, combined studies) or placebo (N=132, combined studies). Injection volume was 0.1 mL/injection site, for a dose/injection site in the active treatment groups of 4 Units. Subjects were injected intramuscularly in five sites, 1 in the procerus muscle and 2 in each corrugator supercilii muscle, for a total dose in the active treatment groups of 20 Units.

The co-primary efficacy endpoints were the investigator’s rating of glabellar line severity at maximum frown and the subject’s global assessment of change in appearance of glabellar lines, both at Day 30 post-injection. For the investigator rating, using a 4-point grading scale (0=none, 3=severe) a responder was defined as having a severity grade of 0 or 1. For the subject’s global assessment of change, the ratings were from +4 (complete improvement) to -4 (very marked worsening). A responder was defined as having a grade of at least +2 (moderate improvement). After completion of the randomized studies, subjects were offered participation in an open label, repeat treatment study to assess the safety of repeated treatment sessions.

The combined results of these two efficacy studies are presented here. The mean age was 46 years, with 32 subjects (6%) ≥65 years of age. Most of the subjects were women (82%), and White (84%). At baseline, 210 subjects (39%) had glabellar line severity scores at rest of moderate or severe.

In these studies, the severity of glabellar lines was reduced for up to 120 days in the BOTOX Cosmetic group compared to the placebo group as measured both by investigator rating of glabellar line severity at maximum frown (Table 8), and by subject’s global assessment of change in appearance of glabellar lines (Table 9).

Table 8: Investigator’s Assessment of Glabellar Line Severity at Maximum Frown – Responder Rates (% and Number of Subjects with Severity of None or Mild)
Day | BOTOX Cosmetic | Placebo | Differencea
7 | 74% 299/405 | 6% 8/132 | 68% (62, 74)
30b | 80% 325/405 | 3% 4/132 | 77% (72, 82)
60 | 70% 283/403 | 2% 2/130 | 69% (64, 74)
90 | 48% 192/403 | 2% 3/128 | 45% (40, 51)
120 | 25% 102/403 | 2% 2/128 | 24% (19, 29)

a 95% confidence intervals are shown in parenthesis

b Day 30: Co-Primary Efficacy Time point, p<0.001

Table 9: Subject’s Assessment of Change in Appearance of Glabellar Lines – Responder Rates (% and Number of Subjects with at Least Moderate Improvement)
Day | BOTOX Cosmetic | Placebo | Differencea
7 | 82% 334/405 | 9% 12/132 | 73% (68, 80)
30b | 89% 362/405 | 7% 9/132 | 83% (77, 88)
60 | 82% 330/403 | 4% 5/130 | 78% (73, 83)
90 | 63% 254/403 | 3% 4/128 | 60% (54, 66)
120 | 39% 157/403 | 1% 1/128 | 38% (33, 43)

a 95% confidence intervals are shown in parenthesis

b Day 30: Co-Primary Efficacy Time point, p<0.001

In the subset of subjects with resting severity scores of moderate or severe, the investigator assessment of a resting severity of mild or none at Day 30 was also achieved by more BOTOX Cosmetic treated subjects (74%, 119/161) than placebo treated subjects (20%, 10/49).

Analysis of the limited number of subjects 65 years or older suggested a lower treatment-associated response compared to subjects less than 65 years of age (Table 10).

Table 10: Investigator’s and Subject’s Assessment – Responder Rates for Subjects <65 and ≥65 Years of Age at Day 30
Assessment | Age Group | BOTOX Cosmetic (N=405) | Placebo (N=132) | Differencea
Investigators (maximal frown) | <65 | 83% 316/382 | 2% 2/123 | 81% (77, 86)
Subjects | <65 | 91% 346/382 | 7% 8/123 | 84% (79, 90)
Investigators (maximal frown) | ≥65 | 39% 9/23 | 22% 2/9 | 17% (-17, 51)
Subjects | ≥65 | 70% 16/23 | 11% 1/9 | 58% (31, 86)

a 95% confidence intervals are shown in parenthesis

Exploratory analyses by gender suggested that responder rates in the BOTOX Cosmetic treated group were higher for women than for men for both the investigator assessment (Day 30; 85% of 334 women, 59% of 71 men) and the Subject Assessment (Day 30; 93% of women, 72% of men). In the limited number of subjects that identified as other races (n=64 in the BOTOX Cosmetic treated group) the responder rates were similar to those observed in White subjects.

14.2 Lateral Canthal Lines

Two multicenter, randomized, double-blind, placebo-controlled studies evaluated BOTOX Cosmetic (N=833, randomized to receive any BOTOX Cosmetic treatment or N=529 randomized to receive placebo) for the temporary improvement in the appearance of moderate to severe lateral canthal lines (LCL). Study 1 assessed BOTOX Cosmetic treatment of LCL alone; Study 2 also assessed simultaneous treatment of LCL and glabellar lines (GL). Both studies enrolled healthy adults with moderate to severe LCL at maximum smile at baseline; Study 2 also required subjects to have moderate to severe GL at maximum frown at baseline.

In the 5-month Study 1, subjects were randomized to receive a single blinded treatment of 24 Units/0.6 mL (12 Units per side) consisting of 4 Units/0.1 mL into 3 sites of each orbicularis oculi muscle with either BOTOX Cosmetic (N=222) or placebo (N=223).

In the 7-month Study 2, subjects were randomized to receive either BOTOX Cosmetic in the LCL region and placebo in the GL region (24 Units; N=306), or BOTOX Cosmetic in the LCL and GL regions (44 Units [24 Units for LCL and 20 Units for GL]; N=305), or placebo in the LCL and GL regions (0 Units; N=306). Subjects received the same 24 Units regimen for LCL as in Study 1, and the labeled 20 Units (5 injections, 4 Units per site) for GL. Subjects received the same treatment at days 1 and 120.

The primary efficacy measure was the assessment of LCL severity at maximum smile using the 4-point Facial Wrinkle Scale with Photonumeric Guide (FWS; 0=none, 1= mild, 2=moderate, 3=severe). The FWS assessment was performed independently by both investigators and subjects. The primary timepoint was day 30 following the first treatment, as compared to baseline.

The primary efficacy response definition was a composite ≥2-grade improvement from baseline in LCL severity at maximum smile, assessed by both investigator and subject on a per-subject basis. For Studies 1 and 2, the proportion of responders was statistically significant favoring BOTOX Cosmetic (24 Units [LCL alone] and 44 Units [LCL and GL]) compared to placebo at day 30 (Table 11).

Table 11: Studies 1 and 2: Composite Investigator and Subject Assessment of LCL at Maximum Smile at Day 30 – Responder Rates (% and Number of Subjects Achieving ≥2-Grade Improvement from Baseline)
Study | BOTOX Cosmetic 24 Units | BOTOX Cosmetic 24 Units LCL and 20 Units GL | Placebo
Study 1 | 26.1% 58/222 | - | 1.3% 3/223
Study 2 | 20.3% 62/306 | 21.3% 65/305 | 0.0% 0/306

The secondary endpoint of a responder defined as achieving a grade of none or mild for Study 1 as measured by the investigator is presented in Figure 7 below.

Figure 7: Percentage of Subjects with Treatment Success (% of Subjects achieving None or Mild from Baseline) by Visit (Study 1)

14.3 Forehead Lines

Two multicenter, randomized, double-blind, placebo-controlled studies evaluated BOTOX Cosmetic (N=921, randomized to receive any BOTOX Cosmetic treatment or N=257, randomized to receive placebo) for the temporary improvement in the appearance of moderate to severe forehead lines (FHL).

Study 1 assessed BOTOX Cosmetic treatment of FHL with glabellar lines (GL); Study 2 also assessed simultaneous treatment of FHL, GL, and lateral canthal lines [LCL]. Both studies enrolled healthy adults with moderate to severe FHL at maximum eyebrow elevation at baseline and moderate to severe GL at maximum frown at baseline; Study 2 also required subjects to have moderate to severe LCL at maximum smile at baseline.

In the 12-month Study 1, subjects were randomized to receive BOTOX Cosmetic 20 Units to the frontalis muscle with 20 Units to the glabellar region (for a total of 40 Units) or placebo in both areas.

In the 12-month Study 2, subjects were randomized to receive BOTOX Cosmetic 20 Units to the frontalis muscle, 20 Units to the glabellar region, and 0 Units to the LCL region (for a total of 40 units) or BOTOX Cosmetic 20 Units to the frontalis muscle, 20 Units to the glabellar region, and 24 Units to the LCL region (for a total of 64 Units) or placebo in all three areas.

The primary efficacy measure was the assessment of FHL severity at maximum eyebrow elevation using the 4-point Facial Wrinkle Scale with Photonumeric Guide (FWS; 0=none, 1= mild, 2=moderate, 3=severe). The FWS assessment was performed independently by both investigators and subjects. The primary timepoint was Day 30 following the first treatment.

The primary efficacy response definition was a composite ≥2-grade improvement from baseline in FHL severity at maximum eyebrow elevation, assessed by both investigator and subject on a per-subject basis. For Studies 1 and 2, the proportion of responders was greater in the BOTOX Cosmetic arms compared to placebo at Day 30 (p<0.0001 for Studies 1 and 2) (Table 12).

Table 12: Studies 1 and 2: Composite Investigator and Subject Assessment of FHL Severity at Maximum Eyebrow Elevation at Day 30 – Responder Rates (% and Number of Subjects Achieving ≥2-Grade Improvement from Baseline)
Study | BOTOX Cosmetic (20 Units FHL with 20 Units GL) | BOTOX Cosmetic (20 Units FHL, 20 Units GL, and 24 Units LCL) | Placebo
Study 1 | N=290 61% | - | N=101 0%
Study 2 | N=318 46% | N=313 53% | N=156 1%

A total of 165 and 197 subjects received 3 cycles over 1 year of BOTOX Cosmetic 40 Units (20 Units FHL with 20 Units GL) and 64 Units (20 Units FHL, 20 Units GL, and 24 Units LCL), respectively. The response rate for FHL was similar across all treatment cycles.

The results for a key secondary endpoint of responders achieving a grade of none or mild on investigator ratings at maximum eyebrow elevation of FHL severity are presented below for Studies 1 and 2.

Figure 8: Percentage of Subjects with Treatment Success (Achieving None or Mild FHL from Baseline at Maximum Eyebrow Elevation) by Visit (Study 1)

Figure 9: Percentage of Subjects with Treatment Success (Achieving None or Mild FHL from Baseline at Maximum Eyebrow Elevation) by Visit (Study 2)

The results of the Facial Line Satisfaction Questionnaire are presented in Table 13.

Table 13: Facial Lines Satisfaction Questionnaire Response Frequency at Day 60 (Percentage of Subjects)
 | Study 1 |  | Study 2
 | BOTOX Cosmetic (20 Units FHL with 20 Units GL) N=289 | Placebo N=99 | BOTOX Cosmetic (20 Units FHL with 20 Units GL) N=317 | Placebo N=155
“Very satisfied” | 57% | 1% | 35% | 0%
“Mostly satisfied” | 33% | 0% | 47% | 3%
“Neither dissatisfied nor satisfied” | 4% | 22% | 9% | 23%
“Mostly dissatisfied” | 4% | 21% | 7% | 20%
“Very dissatisfied” | 2% | 56% | 2% | 54%

14.4 Platysma Bands

Two multicenter, randomized, double-blind, placebo-controlled trials (Study M21-309 [NCT04949399] and Study M21-310 [NCT04994535]) evaluated BOTOX Cosmetic (N=408 BOTOX Cosmetic and N=426 placebo) for the temporary improvement in the appearance of moderate to severe platysma bands. Based on baseline severity, subjects were randomized to receive a single treatment of BOTOX Cosmetic (26 Units, 31 Units, or 36 Units), or placebo.

The primary efficacy measure was the assessment of platysma band severity at maximum contraction using the 5-grade clinician platysma band scale by the investigators, and the 5-grade participant platysma band scale by the subjects. For both scales, the 5 grades are 1=Minimal, 2=Mild, 3=Moderate, 4=Severe, 5=Extreme (Table 14). The investigator and subject assessments were performed independently.

Table 14: Platysma Band Severity Grades and Descriptions
Grade | Severity Description
1 | Minimal; no visible neck bands and no impact to jawline definition
2 | Mild; visible neck bands and no impact to jawline definition
3 | Moderate; 1 visible continuous neck band impacting jawline definition
4 | Severe; 2 visible continuous neck bands impacting jawline definition
5 | Extreme; 3 or more visible neck bands impacting jawline definition

The primary timepoint was Day 14 after the first treatment. The studies enrolled healthy adults with moderate to severe platysma bands. In these studies, 94% were female, 91% were White, 5% were Asian, 3% were Black or African American; for ethnicity, 86% identified as not Hispanic or Latino. Subjects were 19 to 82 years old, with a mean age of 49 years.

The primary efficacy endpoint was a multi-component endpoint defined as achievement of Grade 1 or 2 (Minimal or Mild) and at least a 2-grade improvement from baseline in platysma band severity at maximum contraction, assessed by both investigator and subject at Day 14 (Table 15).

Table 15: Studies M21-309 and M21-310: Percentage of Subjects Achieving a Grade 1 or 2 (Minimal or Mild) with ≥ 2-Grade Improvement from Baseline Based on Both Investigator and Subject Assessments of Platysma Band Severity at Maximum Contraction at Day 14
 | Study M21-309 |  |  | Study M21-310
 | BOTOX Cosmetic 26, 31, or 36 Units (N=199) | Placebo (N=209) | Differenced | BOTOX Cosmetic 26, 31, or 36 Units (N=209) | Placebo (N=217) | Differenced
Multi-component Assessmenta | 32% | 2% | 30% (24%, 37%) | 31% | 0% | 31% (24%, 37%)
Individual Components
Investigator Assessmentb | 45% | 4% | - | 42% | 2% | -
Subject Assessmentc | 44% | 4% | - | 40% | 3% | -

1. Grade 1 or 2 (Minimal or Mild) and ≥ 2-grade improvement from baseline at maximum contraction on both the investigator and subject assessments at Day 14.
2. Grade 1 or 2 (Minimal or Mild) and ≥ 2-grade improvement from baseline at maximum contraction on the investigator assessment at Day 14.
3. Grade 1 or 2 (Minimal or Mild) and ≥ 2-grade improvement from baseline at maximum contraction on the subject assessment at Day 14.
4. 95% confidence intervals are shown in parentheses.

The percentages of subjects achieving these endpoints over time are shown in Figure 10 (Study M21-309) and Figure 11 (Study M21-310).

Figure 10: Percentages of Subjects Achieving a Grade 1 or 2 (Minimal or Mild) and at Least 2-Grade Improvement from Baseline Based on Both the Investigator and Subject Assessments of Platysma Band Severity at Maximum Contraction Over Time (Study M21-309)

Figure 11: Percentages of Subjects Achieving a Grade 1 or 2 (Minimal or Mild) and at Least 2-Grade Improvement from Baseline Based on Both the Investigator and Subject Assessments of Platysma Band Severity at Maximum Contraction Over Time (Study M21-310)

The results for Appearance of Neck and Lower Face Questionnaire: Satisfaction (Follow-up) Item 5 at Day 14 secondary efficacy endpoints are presented for Studies M21-309 and M21-310 in Table 16.

Table 16: Studies M21-309 and M21-310: Results for Appearance of Neck and Lower Face Questionnaire: Satisfaction (Follow-up) Item 5 (Satisfaction with Effect of Treatment on Platysma Bands) at Day 14 (Percentage of Subjects)
Responses | Study M21-309 |  | Study M21-310
 | BOTOX Cosmetic 26, 31, or 36 Units (N = 199) | Placebo (N = 209) | BOTOX Cosmetic 26, 31, or 36 Units (N = 209) | Placebo (N = 217)
“Very satisfied” | 31% | 3% | 22% | 2%
“Satisfied” | 34% | 9% | 40% | 10%
“Neither satisfied nor dissatisfied” | 25% | 31% | 25% | 32%
“Dissatisfied” | 7% | 34% | 10% | 29%
“Very dissatisfied” | 2% | 24% | 3% | 27%

16 HOW SUPPLIED/STORAGE AND HANDLING

BOTOX Cosmetic (onabotulinumtoxinA) for injection is a vacuum-dried powder supplied in a single-dose vial in the following sizes:

50 Units: NDC 0023-3919-50

100 Units: NDC 0023-9232-01

BOTOX Cosmetic cartons have features to alert users if contents may have been compromised. Each BOTOX Cosmetic vial label and carton labeling also contain the U.S. License number 1889 [see Dosage and Administration (2.1)].

Do not use the product and contact AbbVie for additional information at 1-800-678-1605 if the labeling is not as described above.

Storage

Store unopened vials of BOTOX Cosmetic in a refrigerator 2°C to 8°C (36ºF to 46ºF). Do not use after the expiration date on the vial. Store reconstituted BOTOX Cosmetic in a refrigerator 2°C to 8°C (36ºF to 46ºF) and administer within 24 hours [see Dosage and Administration (2.3)].

17 PATIENT COUNSELING INFORMATION

Advise the patient to read the FDA-approved patient labeling (Medication Guide).

Provide a copy of the Medication Guide and review the contents with the patient.

Swallowing, Speaking or Breathing Difficulties, or Other Unusual Symptoms

Advise patients to inform their doctor or pharmacist if they develop any unusual symptoms (including difficulty with swallowing, speaking, or breathing), or if any existing symptom worsens [see Boxed Warning and Warnings and Precautions (5.2, 5.7)].

Ability to Operate Machinery or Vehicles

Advise patients that if loss of strength, muscle weakness, blurred vision, or drooping eyelids occur, avoid driving a car or engaging in other potentially hazardous activities.

Ophthalmic Adverse Reactions

Inform patients that BOTOX Cosmetic injection may cause eye dryness. Advise patients to report symptoms of eye dryness (e.g., eye pain, eye irritation, photosensitivity, or changes in vision) to their doctor.

Manufactured by: AbbVie Inc.
1 N Waukegan Rd. North Chicago, IL 60064
U.S. License number 1889

© 2024 AbbVie. All rights reserved.
BOTOX and its design are trademarks of Allergan, Inc., an AbbVie company.

V4.1USPI3919

MEDICATION GUIDE
BOTOX®
BOTOX® Cosmetic
(Boe-tox)
(onabotulinumtoxinA)
for injection, for intramuscular, intradetrusor,
or intradermal use

What is the most important information I should know about BOTOX and BOTOX Cosmetic?
BOTOX and BOTOX Cosmetic may cause serious side effects that can be life threatening, including:

- Problems breathing or swallowing
- Spread of toxin effects

These problems can happen hours, days, to weeks after an injection of BOTOX or BOTOX Cosmetic.
Call your doctor or get medical help right away if you have any of these problems after treatment with BOTOX or BOTOX Cosmetic:

- Problems swallowing, speaking, or breathing. These problems can happen hours, days, to weeks after an injection of BOTOX or BOTOX Cosmetic usually because the muscles that you use to breathe and swallow can become weak after the injection. Death can happen as a complication if you have severe problems with swallowing or breathing after treatment with BOTOX or BOTOX Cosmetic.
  - People with certain breathing problems may need to use muscles in their neck to help them breathe. These people may be at greater risk for serious breathing problems with BOTOX or BOTOX Cosmetic.
  - Swallowing problems may last for several months. People who cannot swallow well may need a feeding tube to receive food and water. If swallowing problems are severe, food or liquids may go into your lungs. People who already have swallowing or breathing problems before receiving BOTOX or BOTOX Cosmetic have the highest risk of getting these problems.
- Spread of toxin effects. In some cases, the effect of botulinum toxin may affect areas of the body away from the injection site and cause symptoms of a serious condition called botulism. The symptoms of botulism include:
  - loss of strength and muscle weakness all over the body
  - double vision, blurred vision and drooping eyelids
  - hoarseness or change or loss of voice (dysphonia)
  - trouble saying words clearly (dysarthria)
  - loss of bladder control
  - trouble breathing
  - trouble swallowing

These symptoms can happen hours, days, to weeks after you receive an injection of BOTOX or BOTOX Cosmetic.
These problems could make it unsafe for you to drive a car or do other dangerous activities. See "What should I avoid while receiving BOTOX or BOTOX Cosmetic?"
There has not been a confirmed serious case of spread of toxin effect away from the injection site when BOTOX has been used at the recommended dose to treat chronic migraine, severe underarm sweating, blepharospasm, or strabismus, or when BOTOX Cosmetic has been used at the recommended dose to treat frown lines, crow’s feet lines, forehead lines, or vertical bands connecting the jaw and neck.

What are BOTOX and BOTOX Cosmetic?
BOTOX is a prescription medicine that is injected into muscles and used:

- to treat overactive bladder symptoms such as a strong need to urinate with leaking or wetting accidents (urge urinary incontinence), a strong need to urinate right away (urgency) and urinating often (frequency) in adults when another type of medicine (anticholinergic) does not work well enough or cannot be taken.
- to treat leakage of urine (incontinence) in adults with overactive bladder due to neurologic disease when another type of medicine (anticholinergic) does not work well enough or cannot be taken.
- to treat overactive bladder due to a neurologic disease in children 5 years of age and older when another type of medicine (anticholinergic) does not work well enough or cannot be taken.
- to prevent headaches in adults with chronic migraine who have 15 or more days each month with headache lasting 4 or more hours each day.
- to treat increased muscle stiffness in people 2 years of age and older with spasticity.
- to treat the abnormal head position and neck pain that happens with cervical dystonia (CD) in adults.
- to treat certain types of eye muscle problems (strabismus) or abnormal spasm of the eyelids (blepharospasm) in people 12 years of age and older.

BOTOX is also injected into the skin to treat the symptoms of severe underarm sweating (severe primary axillary hyperhidrosis) when medicines used on the skin (topical) do not work well enough.

BOTOX Cosmetic is a prescription medicine for adults that is injected into muscles and used for a short period of time (temporary) to improve the look of:

- moderate to severe frown lines between the eyebrows (glabellar lines)
- moderate to severe crow’s feet lines
- moderate to severe forehead lines
- moderate to severe vertical bands connecting the jaw and neck (platysma bands)

You may receive treatment for frown lines, crow’s feet lines, forehead lines, and vertical bands connecting the jaw and neck at the same time.

It is not known whether BOTOX is safe and effective in people younger than:

- 18 years of age for treatment of overactive bladder with urinary incontinence
- 5 years of age for the treatment of overactive bladder due to a neurologic disease
- 18 years of age for treatment of chronic migraine
- 16 years of age for treatment of cervical dystonia
- 18 years of age for treatment of hyperhidrosis
- 12 years of age for treatment of strabismus or blepharospasm
- 2 years of age for treatment of spasticity

BOTOX Cosmetic is not recommended for use in children younger than 18 years of age.
It is not known whether BOTOX and BOTOX Cosmetic are safe and effective to prevent headaches in people with migraine who have 14 or fewer headache days each month (episodic migraine).
It is not known whether BOTOX and BOTOX Cosmetic are safe and effective for severe sweating anywhere other than your armpits.
It is not known if BOTOX Cosmetic is safe and effective for use more than 1 time every 3 months.

Who should not receive BOTOX or BOTOX Cosmetic?
Do not receive BOTOX or BOTOX Cosmetic if you:

- are allergic to any of the ingredients in BOTOX or BOTOX Cosmetic. See the end of this Medication Guide for a complete list of ingredients in BOTOX and BOTOX Cosmetic.
- had an allergic reaction to any other botulinum toxin product such as Myobloc® (rimabotulinumtoxinB), Dysport® (abobotulinumtoxinA), Xeomin® (incobotulinumtoxinA), Jeuveau® (prabotulinumtoxinA-xvfs), Daxxify® (daxibotulinumtoxinA-lanm), or Letybo® (letibotulinumtoxinA-wlbg). This may not be a complete list of all botulinum toxin products.
- have a skin infection at the planned injection site.
- are being treated for urinary incontinence and have a urinary tract infection (UTI).
- are being treated for urinary incontinence and find that you cannot empty your bladder on your own (only applies to people who are not routinely catheterizing).

What should I tell my doctor before receiving BOTOX or BOTOX Cosmetic?
Tell your doctor about all your medical conditions, including if you:

- have a disease that affects your muscles and nerves (such as amyotrophic lateral sclerosis [ALS or Lou Gehrig's disease], myasthenia gravis or Lambert-Eaton syndrome). See "What is the most important information I should know about BOTOX and BOTOX Cosmetic?"
- have allergies to any botulinum toxin product.
- had any side effect from any botulinum toxin product in the past.
- have or have had a breathing problem, such as asthma or emphysema.
- have or have had swallowing problems.
- have or have had bleeding problems.
- have plans to have surgery.
- had surgery on your face.
- have weakness of your forehead muscles, such as trouble raising your eyebrows.
- have drooping eyelids.
- have any other change in the way your face normally looks.
- have symptoms of a urinary tract infection (UTI) and are being treated for urinary incontinence. Symptoms of a urinary tract infection may include pain or burning with urination, frequent urination, or fever.
- have problems emptying your bladder on your own and are being treated for urinary incontinence.
- are pregnant or plan to become pregnant. It is not known if BOTOX or BOTOX Cosmetic can harm your unborn baby.
- are breastfeeding or plan to breastfeed. It is not known if BOTOX or BOTOX Cosmetic passes into breast milk.

Tell your doctor about all the medicines you take, including prescription and over-the-counter medicines, vitamins and herbal supplements. Using BOTOX or BOTOX Cosmetic with certain other medicines may cause serious side effects. Do not start any new medicines until you have told your doctor that you have received BOTOX or BOTOX Cosmetic in the past.
Especially tell your doctor if you:

- have received any other botulinum toxin product in the last four months.
- have received injections of botulinum toxin, such as Myobloc® (rimabotulinumtoxinB), Dysport® (abobotulinumtoxinA), Xeomin® (incobotulinumtoxinA), Jeuveau® (prabotulinumtoxinA-xvfs), Daxxify® (daxibotulinumtoxinA-lanm), or Letybo® (letibotulinumtoxinA-wlbg) in the past. This may not be a complete list of all botulinum toxin products. Be sure your doctor knows exactly which product you received.
- have recently received an antibiotic by injection.
- take muscle relaxants.
- take an allergy or cold medicine.
- take a sleep medicine.
- take anti-platelets (aspirin-like products) or anti-coagulants (blood thinners).

Ask your doctor if you are not sure if your medicine is one that is listed above.
Know the medicines you take. Keep a list of your medicines with you to show your doctor and pharmacist each time you get a new medicine.

How will I receive BOTOX or BOTOX Cosmetic?

- BOTOX or BOTOX Cosmetic is an injection that your doctor will give you.
- BOTOX is injected into your affected muscles, skin, or bladder.
- BOTOX Cosmetic is injected into your affected muscles.
- Your doctor may change your dose of BOTOX or BOTOX Cosmetic, until you and your doctor find the best dose for you.
- Your doctor will tell you how often you will receive your dose of BOTOX or BOTOX Cosmetic injections.

What should I avoid while receiving BOTOX or BOTOX Cosmetic?
BOTOX and BOTOX Cosmetic may cause loss of strength or general muscle weakness, vision problems, or dizziness within hours to weeks of taking BOTOX or BOTOX Cosmetic. If this happens, do not drive a car, operate machinery, or do other dangerous activities. See "What is the most important information I should know about BOTOX and BOTOX Cosmetic?"

What are the possible side effects of BOTOX and BOTOX Cosmetic?
BOTOX and BOTOX Cosmetic can cause serious side effects. See "What is the most important information I should know about BOTOX and BOTOX Cosmetic?"
Other side effects of BOTOX and BOTOX Cosmetic include:

- dry mouth.
- discomfort or pain at the injection site.
- tiredness.
- headache.
- neck pain.
- eye problems: double vision, blurred vision, decreased eyesight, drooping eyelids, swelling of your eyelids, and dry eyes.
- drooping eyebrows.
- urinary tract infection in both children and adults being treated for urinary incontinence.
- painful urination in adults being treated for urinary incontinence.
- bacteria, white blood cells, and blood in the urine of children being treated for urinary incontinence.
- inability to empty your bladder on your own and are being treated for urinary incontinence. If you have difficulty fully emptying your bladder after getting BOTOX, you may need to use disposable self-catheters to empty your bladder up to a few times each day until your bladder is able to start emptying again.
- allergic reactions. Symptoms of an allergic reaction to BOTOX or BOTOX Cosmetic may include: itching, rash, red itchy welts, wheezing, asthma symptoms, or dizziness or feeling faint. Tell your doctor or get medical help right away if you are wheezing or have asthma symptoms, or if you become dizzy or faint.
- upper respiratory tract infection.

Tell your doctor if you have any side effect that bothers you or that does not go away.
These are not all the possible side effects of BOTOX and BOTOX Cosmetic. For more information, ask your doctor or pharmacist.
Call your doctor for medical advice about side effects. You may report side effects to FDA at 1-800-FDA-1088.

General information about the safe and effective use of BOTOX and BOTOX Cosmetic:
Medicines are sometimes prescribed for purposes other than those listed in a Medication Guide. This Medication Guide summarizes the most important information about BOTOX and BOTOX Cosmetic. If you would like more information, talk with your doctor. You can ask your doctor or pharmacist for information about BOTOX and BOTOX Cosmetic that is written for health professionals.

What are the ingredients in BOTOX and BOTOX Cosmetic?
Active ingredient: onabotulinumtoxinA
Inactive ingredients: human albumin and sodium chloride

Manufactured by: AbbVie Inc.
1 N Waukegan Rd. North Chicago, IL 60064
U.S. License Number 1889
© 2024 AbbVie. All rights reserved. BOTOX and its design are trademarks of Allergan, Inc., an AbbVie company.
All trademarks are the property of their respective owners.
V8.0MG1145

This Medication Guide has been approved by the U.S. Food and Drug Administration Revised: 10/2024

PRINCIPAL DISPLAY PANEL

NDC 0023-3919-50
BOTOX®
COSMETIC
onabotulinumtoxinA
for Injection
50
Units/vial
Allergan
Aesthetics
an AbbVie company

PRINCIPAL DISPLAY PANEL

NDC 0023-9232-01
BOTOX®
COSMETIC
onabotulinumtoxinA
for Injection
100
Units/vial
Allergan
Aesthetics
an AbbVie company